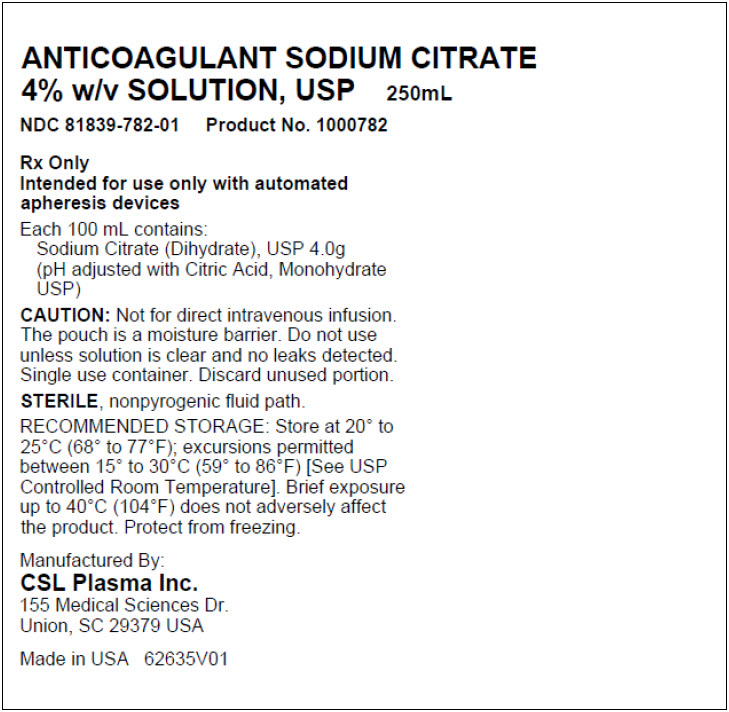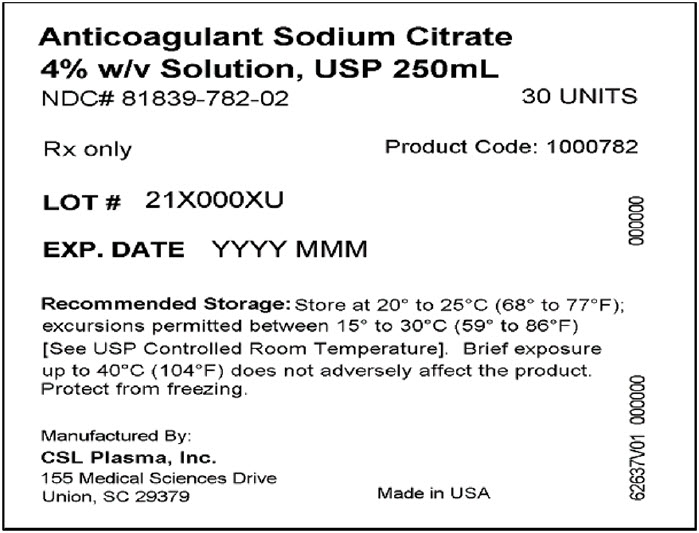 DRUG LABEL: Anticoagulant Sodium Citrate
NDC: 81839-782 | Form: SOLUTION
Manufacturer: CSL Plasma Inc.
Category: prescription | Type: HUMAN PRESCRIPTION DRUG LABEL
Date: 20240110

ACTIVE INGREDIENTS: Trisodium Citrate Dihydrate 40 mg/1 mL
INACTIVE INGREDIENTS: Water; Citric Acid monohydrate

HIGHLIGHTS OF PRESCRIBING INFORMATION

These highlights do not include all the information needed to use ANTICOAGULANT SODIUM CITRATE 4 % W/V SOLUTION USP safely and effectively. See full prescribing information for ANTICOAGULANT SODIUM CITRATE 4 % W/V SOLUTION USP.
ANTICOAGULANT SODIUM CITRATE 4 % W/V SOLUTION USP
Sterile Fluid
PVC Bag
Initial U.S. Approval: 1978

1. INDICATIONS AND USAGE

ANTICOAGULANT SODIUM CITRATE 4% W/V SOLUTION USP is intended for use only for the anticoagulation of whole blood as part of automated apheresis procedures. (1)

2. DOSAGE AND ADMINISTRATION

- ANTICOAGULANT SODIUM CITRATE 4% W/V SOLUTION USP is added to tubing sets during apheresis procedures. (2)
- ANTICOAGULANT SODIUM CITRATE 4% W/V SOLUTION USP may only be used with apheresis devices. For instructions on the use of the solution see the apheresis device operator's manual. (2.1)
- Follow the directions for connecting the ANTICOAGULANT SODIUM CITRATE 4% W/V SOLUTION USP bag to the apheresis system. (2.2)

3. DOSAGE FORMS AND STRENGTHS

- 250 mL sterile fluid in a PVC bag. (3)

4. CONTRAINDICATIONS

- DO NOT INFUSE ANTICOAGULANT SODIUM CITRATE 4% W/V SOLUTION USP DIRECTLY TO THE DONOR. (4)

5. WARNINGS AND PRECAUTIONS

- Verify that the ANTICOAGULANT SODIUM CITRATE 4% W/V SOLUTION USP has been securely attached to the anticoagulant (AC) line on the system tubing set. Use aseptic technique throughout all procedures to ensure donor safety and quality.
- Single-use container, do not reuse. Discard any unused or partially used product.
- Rx only (5)

6. ADVERSE REACTIONS

Citrate reactions or toxicity may occur with the infusion and return of blood containing citrate anticoagulant. The recipient of the blood containing citrate should be monitored for the signs and symptoms of citrate toxicity. (6)

To report SUSPECTED ADVERSE REACTIONS, contact CSL Plasma Inc. at 1-833-275-0044 or FDA at 1-800-FDA-1088 or www.fda.gov/medwatch.

8. USE IN SPECIFIC POPULATIONS

ANTICOAGULANT SODIUM CITRATE 4% W/V SOLUTION USP has not been studied in controlled clinical trials with specific populations.

FULL PRESCRIBING INFORMATION

1. INDICATIONS AND USAGE

ANTICOAGULANT SODIUM CITRATE 4% W/V SOLUTION USP is intended for use only for the anticoagulation of whole blood as part of automated apheresis procedures. [See Dosage and Administration (2).]

2. DOSAGE AND ADMINISTRATION

2.1. General Dosing Information

ANTICOAGULANT SODIUM CITRATE 4% W/V SOLUTION USP is added to tubing sets during apheresis procedures. The solution bag is connected to the tubing set in an apheresis collection. The recommended dose is determined by the apheresis device and metered into the tubing set by the apheresis device. It is not intended for direct intravenous infusion.

For instructions on the use of the solution with the apheresis device and tubing set, see the device operator's manual.

2.2. Administration

- Ensure solution is the ANTICOAGULANT SODIUM CITRATE 4% W/V SOLUTION USP and is within the expiration date
- Inspect the bag. Do not use if the container is damaged, leaking, or if there is any visible sign of deterioration
- Use only if solution is clear and free of particulate matter
- Protect from sharp objects.

Directions for connecting the ANTICOAGULANT SODIUM CITRATE 4% W/V SOLUTION USP bag to the apheresis device.

At the prompt to connect anticoagulant to the apheresis device tubing set:

1. Remove the overwrap by pulling down at the notch, and remove the ANTICOAGULANT SODIUM CITRATE 4% W/V SOLUTION USP bag.
2. Before use, perform the following checks [see Warnings and Precautions (5)]:
  - Check for leaks by gently squeezing the bag. If leaks are found, discard the bag
  - Ensure that the solution is the ANTICOAGULANT SODIUM CITRATE 4% W/V SOLUTION USP and is within the expiration date
  - Inspect the solution in good light. Bags showing cloudiness, haze, or particulate matter should not be used
3. Remove the twist off port on the bag
4. Connect the bag to the apheresis device tubing set using aseptic technique and hang the solution
5. Proceed according to the apheresis device operator's manual

Drug products should be inspected visually for particulate matter and discoloration prior to administration, whenever the solution and container permit.

3. DOSAGE FORMS AND STRENGTHS

250 mL ANTICOAGULANT SODIUM CITRATE 4% W/V SOLUTION USP is a sterile solution in a PVC bag. Each 100 mL contains: Sodium Citrate (dihydrate) 4.0 g; Water for Injection to 100 mL, (pH adjusted with citric acid). Approximate millimoles of Sodium Citrate: 13.6.

4. CONTRAINDICATIONS

DO NOT INFUSE ANTICOAGULANT SODIUM CITRATE 4% W/V SOLUTION USP DIRECTLY TO THE DONOR.

5. WARNINGS AND PRECAUTIONS

- Verify that the ANTICOAGULANT SODIUM CITRATE 4% W/V SOLUTION USP has been securely attached to the anticoagulant (AC) line on the system tubing set. Use aseptic technique throughout all procedures to ensure donor safety and quality.
- Single-use container. Do not reuse. Discard any unused or partially used product.
- Rx only

6. ADVERSE REACTIONS

Citrate reactions or toxicity may occur with the infusion of blood products to patient and return of blood containing citrate anticoagulant to donors. The recipient of the blood containing citrate should be monitored for the signs and symptoms of citrate toxicity. The signs and symptoms of citrate toxicity begin with paresthesia, a "tingling" sensation around the mouth or in the extremities, followed by severe reactions that are characterized by hypotension and possible cardiac arrhythmia. Citrate toxicity may occur more frequently in patients who are hypothermic, have impaired liver or renal function, or have low calcium levels because of an underlying disease.

8. USE IN SPECIFIC POPULATIONS

ANTICOAGULANT SODIUM CITRATE 4% W/V SOLUTION USP has not been adequately studied in controlled clinical trials with specific populations.

11. DESCRIPTION

ANTICOAGULANT SODIUM CITRATE 4% W/V SOLUTION USP is designed to be metered by an apheresis device in apheresis procedures, to prevent platelet activation and coagulation as blood moves throughout the extracorporeal unit (tubing set) in an apheresis procedure.

The solution is sterile and non-pyrogenic, and it contains no bacteriostatic or antimicrobial agents. Sterilized with steam.

The formulas of the active ingredients are provided in Table 1.

Table 1: Active Ingredients
Ingredients | Molecular Formula | Molecular Weight
Sodium Citrate Dihydrate | C6H9Na3O9 | 294.10
Water for Injection | H2O | 18.00

Each 100 mL of ANTICOAGULANT SODIUM CITRATE 4% W/V SOLUTION USP contains:

Sodium Citrate (dihydrate) 4.0 g; and Water for Injection to 100 mL (pH adjusted with citric acid). Approximate millimoles of sodium citrate: 13.6.

The PVC bag is not made with natural rubber latex.

The bag contains materials that have been tested to demonstrate the suitability of the container for storing pharmaceutical solutions. The bag is nontoxic and biologically inert. The bag-solution unit is a closed system and is not dependent upon entry of external air during administration. The bag is overwrapped to provide protection from the physical environment and to provide an additional moisture barrier when necessary.

12. CLINICAL PHARMACOLOGY

12.1. Mechanism of Action

ANTICOAGULANT SODIUM CITRATE 4% W/V SOLUTION USP acts as an extracorporeal anticoagulant by binding the free calcium in the blood. Calcium is a necessary co-factor to several steps in the clotting cascade. The following ingredients are key components of the solution:

- Citric acid for pH regulation
- Sodium Citrate anticoagulant

This solution has no pharmacological effect.

16. HOW SUPPLIED/STORAGE AND HANDLING

ANTICOAGULANT SODIUM CITRATE 4% W/V SOLUTION USP is a clear solution supplied in sterile and non-pyrogenic PVC bags. The bags are packaged 30 bags per case.

SIZE | CATALOG NUMBER | NDC NUMBER
250 mL | 1000782 | Bag: 81839-782-01 Case: 81839-782-02

STORAGE

Store at 20° to 25°C (68°to 77°F); excursions permitted between 15° to 30°C (59° to 86°F) [See USP Controlled Room Temperature]. Brief exposure up to 40°C (104°F) does not adversely affect the product.

Protect from freezing.

Issued: 05/2022

Manufactured By:
CSL Plasma, Inc.
155 Medical Sciences Drive
Union, SC 29379

PRINCIPAL DISPLAY PANEL - 250 mL Bag Label

ANTICOAGULANT SODIUM CITRATE
4% w/v SOLUTION, USP
250mL
NDC 81839-782-01
Product No. 1000782

Rx Only
Intended for use only with automated
apheresis devices

Each 100 mL contains:
Sodium Citrate (Dihydrate), USP 4.0g
(pH adjusted with Citric Acid, Monohydrate
USP)

CAUTION: Not for direct intravenous infusion.
The pouch is a moisture barrier. Do not use
unless solution is clear and no leaks detected.
Single use container. Discard unused portion.

STERILE, nonpyrogenic fluid path.

RECOMMENDED STORAGE: Store at 20° to
25°C (68° to 77°F); excursions permitted
between 15° to 30°C (59° to 86°F) [See USP
Controlled Room Temperature]. Brief exposure
up to 40°C (104°F) does not adversely affect
the product. Protect from freezing.

Manufactured By:
CSL Plasma Inc.
155 Medical Sciences Dr.
Union, SC 29379 USA

Made in USA
62635V01

PRINCIPAL DISPLAY PANEL - 250 mL Carton Label

Anticoagulant Sodium Citrate
4% w/v Solution, USP 250mL
NDC# 81839-782-02
30 UNITS

Rx only
Product Code: 1000782

LOT # 21X000XU

EXP. DATE YYYY MMM

Recommended Storage: Store at 20° to 25°C (68° to 77°F);
excursions permitted between 15° to 30°C (59° to 86°F)
[See USP Controlled Room Temperature]. Brief exposure
up to 40°C (104°F) does not adversely affect the product.
Protect from freezing.

Manufactured By:
CSL Plasma Inc.
155 Medical Sciences Drive
Union, SC 29379

Made in USA

62635V01 000000

000000